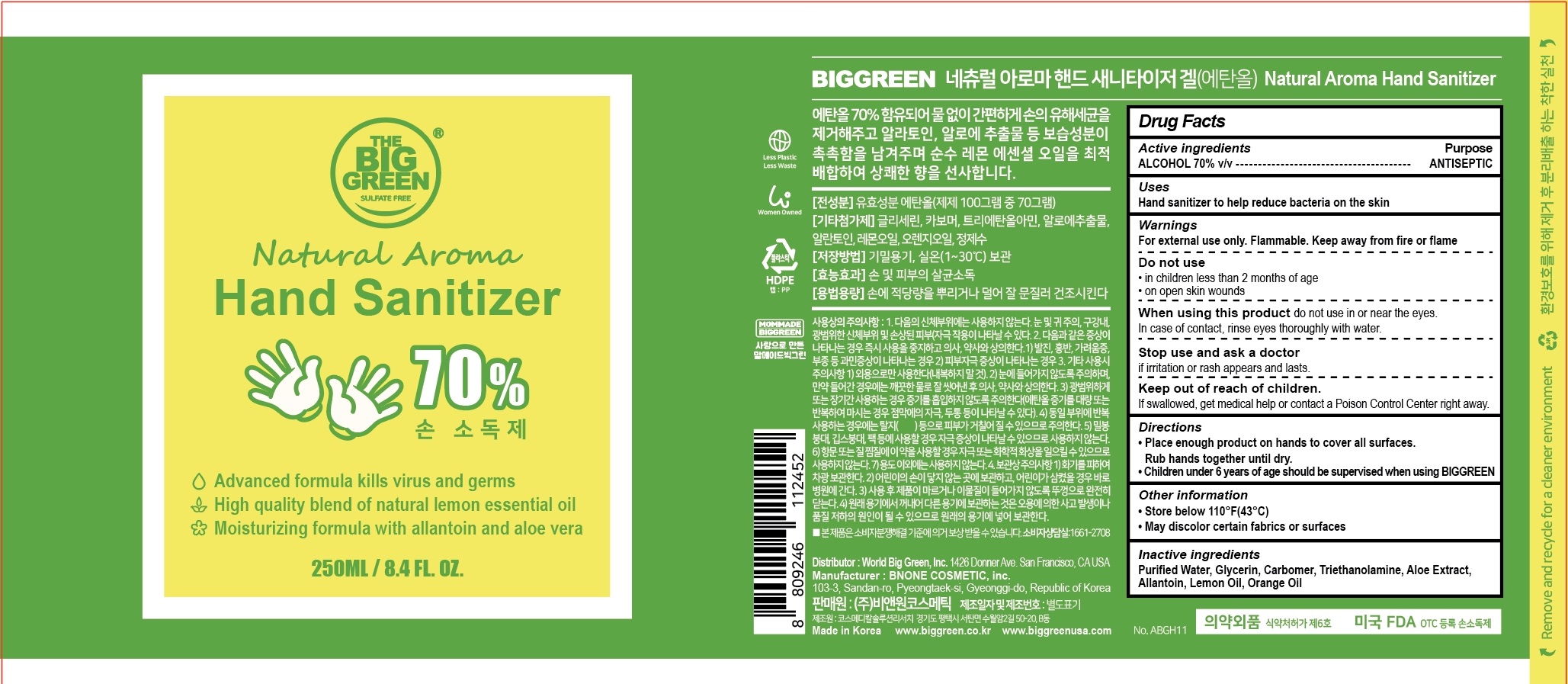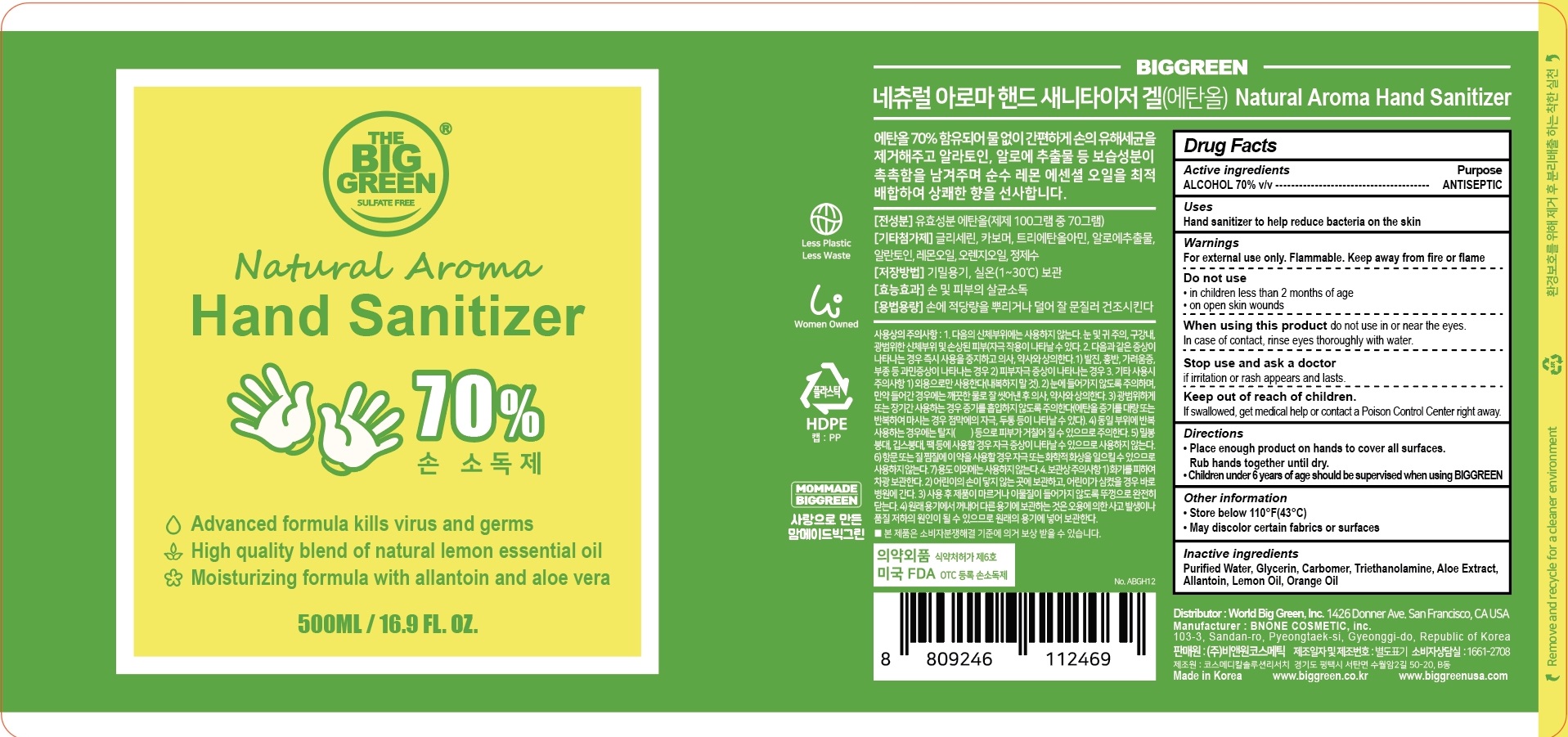 DRUG LABEL: Natural Aroma Hand Sanitizer
NDC: 76768-010 | Form: GEL
Manufacturer: World Big Green, Inc.
Category: otc | Type: HUMAN OTC DRUG LABEL
Date: 20200825

ACTIVE INGREDIENTS: ALCOHOL 70 mL/100 mL
INACTIVE INGREDIENTS: Water; Glycerin; CARBOMER HOMOPOLYMER, UNSPECIFIED TYPE; TROLAMINE; ALOE VERA LEAF; Lemon Oil; Orange Oil

ACTIVE INGREDIENT

ALCOHOL 70% v/v

INACTIVE INGREDIENTS

Purified Water, Glycerin, Carbomer, Triethanolamine, Aloe Extract, Allantoin, Lemon Oil, Orange Oil

PURPOSE

ANTISEPTIC

WARNINGS

For external use only. Flammable. Keep away from fire or flame

----------------------------------------------------------------------------
Do not use
• in children less than 2 months of age
• on open skin wounds
----------------------------------------------------------------------------
When using this product do not use in or near the eyes. In case of contact, rinse eyes thoroughly with water.
----------------------------------------------------------------------------
Stop use and ask a doctor if irritation or rash appears and lasts.

KEEP OUT OF REACH OF CHILDREN

If swallowed, get medical help or contact a Poison Control Center right away.

Uses

Hand sanitizer to help reduce bacteria on the skin

Directions

• Place enough product on hands to cover all surfaces. Rub hands together until dry.

• Children under 6 years of age should be supervised when using BIGGREEN

Other information

• Store below 110°F(43°C)

• May discolor certain fabrics or surfaces